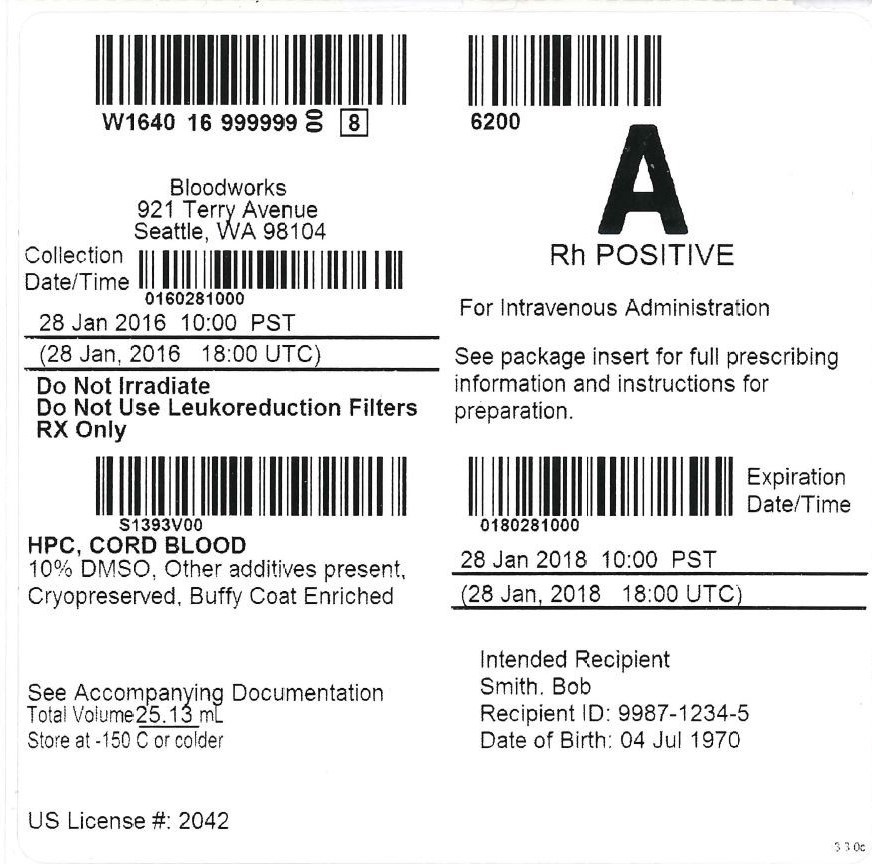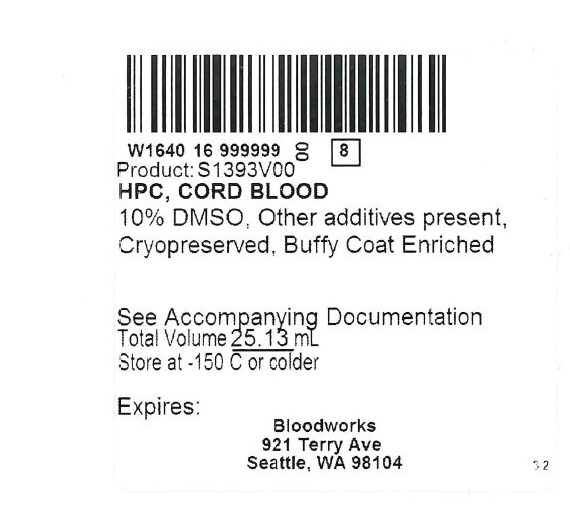 DRUG LABEL: HPC, Cord Blood
NDC: W1640-S1393 | Form: INJECTION
Manufacturer: Bloodworks
Category: other | Type: LICENSED MINIMALLY MANIPULATED CELLS LABEL
Date: 20160128

ACTIVE INGREDIENTS: HUMAN CORD BLOOD HEMATOPOIETIC PROGENITOR CELL 500000000 1/25 mL
INACTIVE INGREDIENTS: DIMETHYL SULFOXIDE; DEXTRAN 40

HIGHLIGHTS OF PRESCRIBING INFORMATION

These highlights do not include all the information needed to use HPC, Cord Blood safely and effectively. See full prescribing information for HPC, Cord Blood.
HPC, Cord Blood
Injectable Suspension for Intravenous Use
Initial U.S. Approval: 2016

WARNING: FATAL INFUSION REACTIONS, GRAFT VERSUS HOST DISEASE, ENGRAFTMENT SYNDROME, AND GRAFT FAILURE

See full prescribing information for complete boxed warning.

- Fatal infusion reactions: Monitor patients during infusion and discontinue for severe reactions. (5.1, 5.2)
- Graft-vs-host disease (GVHD): GVHD may be fatal. Administration of immunosuppressive therapy may decrease risk of GVHD. (5.3)
- Engraftment Syndrome: Engraftment syndrome may be fatal. Treat engraftment syndrome promptly with corticosteroids. (5.4)
- Graft Failure: Graft failure may be fatal. Monitor patients for laboratory evidence of hematopoietic recovery. (5.5)

1 INDICATIONS AND USAGE

HPC (Hematopoietic Progenitor Cell), Cord Blood is an allogeneic cord blood hematopoietic progenitor cell therapy indicated for use in unrelated donor hematopoietic progenitor cell transplantation procedures in conjunction with an appropriate preparative regimen for hematopoietic and immunologic reconstitution in patients with disorders affecting the hematopoietic system that are inherited, acquired, or result from myeloablative treatment. (1)

The risk benefit assessment for an individual patient depends on the patient characteristics, including disease, stage, risk factors, and specific manifestations of the disease, on characteristics of the graft, and on other available treatments or types of hematopoietic progenitor cells. (1)

2 DOSAGE AND ADMINISTRATION

- For intravenous use only.
- Do not irradiate.
- Unit selection and administration of HPC, Cord Blood should be done under the direction of a physician experienced in hematopoietic progenitor cell transplantation. (2)
- The recommended minimum dose is 2.5 x 10^7 nucleated cells/kg at cryopreservation. (2.1)
- Do not administer HPC, Cord Blood through the same tubing as other products except for normal saline. (2.3)

3 DOSAGE FORMS AND STRENGTHS

Each unit contains a minimum of 5 x 10^8 nucleated cells with at least 1.25 x 10^6 viable CD34+ cells at the time of cryopreservation. The exact pre-cryopreservation nucleated cell content of each unit is provided on the container label and accompanying records. (3)

4 CONTRAINDICATIONS

None (4)

5 WARNINGS AND PRECAUTIONS

- Hypersensitivity Reactions (5.1)
- Infusion Reactions (5.2)
- Graft-versus-Host Disease (5.3)
- Engraftment Syndrome (5.4)
- Graft Failure (5.5)
- Malignancies of Donor Origin (5.6)
- Transmission of Serious Infections (5.7)
- Transmission of Rare Genetic Diseases (5.8)

6 ADVERSE REACTIONS

Mortality, from all causes, at 100 days post-transplant was 25%. (6.1)

The most common infusion-related adverse reactions (≥ 5%) are hypertension, vomiting, nausea, bradycardia, and fever. (6.1)

To report SUSPECTED ADVERSE REACTIONS, contact Bloodworks at 1-206-321-3108 or FDA at 1-800-FDA-1088 or www.fda.gov/medwatch.

FULL PRESCRIBING INFORMATION

WARNING: FATAL INFUSION REACTIONS, GRAFT VERSUS HOST DISEASE, ENGRAFTMENT SYNDROME, AND GRAFT FAILURE

Fatal infusion reactions: HPC, Cord Blood administration can result in serious, including fatal, infusion reactions. Monitor patients and discontinue HPC, Cord Blood infusion for severe reactions. [See Warnings and Precautions (5.1, 5.2)]

Graft-versus-host disease (GVHD): GVHD is expected after administration of HPC, Cord Blood, and may be fatal. Administration of immunosuppressive therapy may decrease the risk of GVHD. [See Warnings and Precautions (5.3)]

Engraftment Syndrome: Engraftment syndrome may progress to multiorgan failure and death. Treat engraftment syndrome promptly with corticosteroids. [See Warnings and Precautions (5.4)]

Graft Failure: Graft failure may be fatal. Monitor patients for laboratory evidence of hematopoietic recovery. Prior to choosing a specific unit of HPC, Cord Blood unit, consider testing for HLA antibodies to identify patients who are alloimmunized. [See Warnings and Precautions (5.5)]

1 INDICATIONS AND USAGE

HPC (Hematopoietic Progenitor Cell), Cord Blood, is an allogeneic cord blood hematopoietic progenitor cell therapy indicated for use in unrelated donor hematopoietic progenitor cell transplantation procedures in conjunction with an appropriate preparative regimen for hematopoietic and immunologic reconstitution in patients with disorders affecting the hematopoietic system that are inherited, acquired, or result from myeloablative treatment.

The risk benefit assessment for an individual patient depends on the patient characteristics, including disease, stage, risk factors, and specific manifestations of the disease, on characteristics of the graft, and other available treatments or types of hematopoietic progenitor cells.

2 DOSAGE AND ADMINISTRATION

- For intravenous use only.
- Do not irradiate.

Unit selection and administration of HPC, Cord Blood, should be done under the direction of a physician experienced in hematopoietic progenitor cell transplantation.

2.1 Dosing

The recommended minimum dose is 2.5 x 10^7 nucleated cells/kg at cryopreservation. Multiple units may be required in order to achieve the appropriate dose.

Matching for at least 4 of 6 HLA-A antigens, HLA-B antigens, and HLA-DRB1 alleles is recommended. The HLA typing and nucleated cell content for each individual unit of HPC, Cord Blood are documented on the container label and/or in accompanying records.

2.2 Preparation for Infusion

HPC, Cord Blood should be prepared by a trained healthcare professional.

- Do not irradiate HPC, Cord Blood.
- See the appended detailed instructions for preparation of HPC, Cord Blood for infusion.
- HPC, Cord Blood may be stored at 2 to 8°C for up to 4 hours from time of thaw. [See Instructions for Preparation for Infusion]
- The recommended limit on DMSO administration is 1 gram per kg body weight per day. [See Warnings and Precautions (5.2) and Overdosage (10)]

2.3 Administration

HPC, Cord Blood should be administered under the supervision of a qualified healthcare professional experienced in hematopoietic progenitor cell transplantation.

1. Confirm the identity of the patient for the specified unit of HPC, Cord Blood prior to administration.
2. Confirm that emergency medications are available for use in the immediate area.
3. Ensure the patient is hydrated adequately.
4. Premedicate the patient 30 to 60 minutes before the administration of HPC, Cord Blood. Premedication should include any or all of the following: antipyretic, histamine antagonists, and corticosteroids.
5. Inspect the product for any abnormalities, such as unusual particulates, and for breaches of container integrity prior to administration. Prior to infusion, discuss all such product irregularities with the laboratory issuing the product for infusion.
6. Administer HPC, Cord Blood by intravenous infusion. Do not administer in the same tubing concurrently with products other than 0.9% Sodium Chloride, Injection (USP). HPC, Cord Blood may be infused through a 170 to 260 micron filter designed to remove clots. Do NOT use a filter designed to remove leukocytes.
7. HPC, Cord Blood should be infused over 15 to 60 minutes depending on the volume of the product and the weight of the patient. The rate of infusion should not exceed a maximum of 5 milliliters per kilogram per hour. The infusion rate should be reduced if the fluid load is not tolerated. The infusion should be discontinued in the event of an allergic reaction or if the patient develops a moderate to severe infusion reaction. [See Warnings and Precautions (5.2) and Adverse Reactions (6)]
8. Monitor the patient for adverse reactions during, and for at least six hours after, administration. Because HPC, Cord Blood contains lysed red blood cells that may cause renal failure, careful monitoring of urine output is also recommended.

NOTE: If product is being prepared for a multi-unit infusion, infuse units independently. Should a reaction occur, appropriately manage the reaction before the second unit is thawed for infusion.

3 DOSAGE FORMS AND STRENGTHS

Each HPC, Cord Blood unit contains a minimum of 5.0 x 10^8 total nucleated cells with a minimum of 1.25 x 10^6 viable CD34+ cells, suspended in 10% dimethyl sulfoxide (DMSO) and 1% Dextran 40, at the time of cryopreservation.

The exact pre-cryopreservation nucleated cell content is provided on the container label and in accompanying records.

4 CONTRAINDICATIONS

None

5 WARNINGS AND PRECAUTIONS

5.1 Hypersensitivity Reactions

Allergic reactions may occur with infusion of HPC, Cord Blood. Reactions include bronchospasm, wheezing, angioedema, pruritus, and hives. [See Adverse Reactions (6)]. Serious hypersensitivity reactions, including anaphylaxis, also have been reported. These reactions may be due to dimethyl sulfoxide (DMSO), Dextran 40, hydroxyethyl starch, or a plasma component of HPC, Cord Blood.

HPC, Cord Blood may contain residual antibiotics if the cord blood donor was exposed to antibiotics in utero. Patients with a history of allergic reactions to antibiotics should be monitored for allergic reactions following HPC, Cord Blood administration.

5.2 Infusion Reactions

Infusion reactions are expected to occur and include nausea, vomiting, fever, rigors or chills, flushing, dyspnea, hypoxemia, chest tightness, hypertension, tachycardia, bradycardia, dysguesia, hematuria, and mild headache. Premedication with antipyretic, histamine antagonists, and corticosteroids may reduce the incidence and intensity of infusion reactions.

Severe reactions, including respiratory distress, severe bronchospasm, severe bradycardia with heart block or other arrhythmias, cardiac arrest, hypotension, hemolysis, elevated liver enzymes, renal compromise, encephalopathy, loss of consciousness, and seizure also may occur. Many of these reactions are related to the amount of DMSO administered. Minimizing the amount of DMSO administered may reduce the risk of such reactions, although idiosyncratic responses may occur even at DMSO doses thought to be tolerated. The actual amount of DMSO depends on the method of preparation of the product for infusion. Limiting the amount of DMSO infused to no more than 1 gram per kilogram per day is recommended. [See Overdosage (10)]

Infusion reactions may begin within minutes of the start of infusion of HPC, Cord Blood, although symptoms may continue to intensify and not peak for several hours after completion of the infusion. Monitor the patient closely during this period. When a reaction occurs, discontinue the infusion and institute supportive care as needed.

If infusing more than one unit of HPC, Cord Blood on the same day, do not administer subsequent units until all signs and symptoms of infusion reactions from the prior unit have resolved.

5.3 Graft-versus-Host Disease

Acute and chronic graft-versus-host disease (GVHD) may occur in patients who have received HPC, Cord Blood. Classic acute GVHD is manifested by fever, rash, elevated bilirubin and liver enzymes, and diarrhea. Patients transplanted with HPC, Cord Blood should receive immunosuppressive drugs to decrease the risk of GVHD. [See Adverse Reactions (6.1)]

5.4 Engraftment Syndrome

Engraftment syndrome is manifested as unexplained fever and rash in the peri-engraftment period. Patients with engraftment syndrome also may have unexplained weight gain, hypoxemia, and pulmonary infiltrates in the absence of fluid overload or cardiac disease. If untreated, engraftment syndrome may progress to multiorgan failure and death. Once engraftment syndrome is recognized, begin treatment with corticosteroids to ameliorate the symptoms. [See Adverse Reactions (6.1)]

5.5 Graft Failure

Primary graft failure, which may be fatal, is defined as failure to achieve an absolute neutrophil count greater than 500 per microliter blood by Day 42 after transplantation. Immunologic rejection is the primary cause of graft failure. Patients should be monitored for laboratory evidence of hematopoietic recovery. Consider testing for HLA antibodies in order to identify patients who are alloimmunized prior to transplantation and to assist with choosing a unit with a suitable HLA type for the individual patient. [See Adverse Reactions (6.1)]

5.6 Malignancies of Donor Origin

Patients who have undergone HPC, Cord Blood transplantation may develop post-transplant lymphoproliferative disorder (PTLD), manifested as a lymphoma-like disease favoring non-nodal sites. PTLD is usually fatal if not treated.

The incidence of PTLD appears to be higher in patients who have received antithymocyte globulin. The etiology is thought to be donor lymphoid cells transformed by Epstein-Barr virus (EBV). Serial monitoring of blood for EBV DNA may be warranted in high-risk groups.

Leukemia of donor origin also has been reported in HPC, Cord Blood recipients. The natural history is presumed to be the same as that for de novo leukemia.

5.7 Transmission of Serious Infections

Transmission of infectious disease may occur because HPC, Cord Blood is derived from human blood. Disease may be caused by known or unknown infectious agents. Donors are screened for increased risk of infection with human immunodeficiency virus (HIV), human T-cell lymphotrophic virus (HTLV), hepatitis B virus (HBV), hepatitis C virus (HCV), T. Pallidum, T. cruzi, West Nile Virus (WNV), transmissible spongiform encephalopathy (TSE) agents, and vaccinia. Donors are also screened for clinical evidence of sepsis, and communicable disease risks associated with xenotransplantation. Maternal blood samples are tested for HIV types 1 and 2, HTLV types I and II, HBV, HCV, T. Pallidum, WNV, and T. cruzi. HPC, Cord Blood is tested for sterility. There may be an effect on the reliability of the sterility test results if the cord blood donor mother was treated with antibiotics. These measures do not totally eliminate the risk of transmitting these or other transmissible infectious diseases and disease agents. Report the occurrence of transmitted infection to Bloodworks at 1-206-321-3108.

Testing is also performed for evidence of donor infection due to cytomegalovirus (CMV).

Test results may be found in accompanying records.

5.8 Transmission of Rare Genetic Diseases

HPC, Cord Blood may transmit rare genetic diseases involving the hematopoietic system for which donor screening and/or testing has not been performed [See Adverse Reactions (6.1)]. Cord blood donors have been screened by family history to exclude inherited disorders of the blood and marrow. HPC, Cord Blood has been tested to exclude donors with sickle cell anemia, and anemias due to abnormalities in hemoglobins C, D, and E. Because of the age of the donor at the time HPC, Cord Blood collection takes place, the ability to exclude rare genetic diseases is severely limited.

6 ADVERSE REACTIONS

Day-100 mortality from all causes was 25%.

The most common infusion-related adverse reactions (≥ 5%) are hypertension, vomiting, nausea, bradycardia, and fever.

6.1 Clinical Trials Experience

Because clinical trials are conducted under widely varying conditions, adverse reaction rates observed in the clinical trials of a drug cannot be directly compared to rates in the clinical trials of another drug and may not reflect the rates observed in practice.

The safety assessment of HPC, Cord Blood is based primarily on review of the data submitted to the FDA dockets from various sources, the dataset for the COBLT Study, and published literature.

Infusion Reactions

The data described in Table 1 reflect exposure to 442 infusions of HPC, Cord Blood (from multiple cord blood banks) in patients treated using a total nucleated cell dose of ≥ 2.5 x 10^7/kg on a single-arm trial or expanded access use (the COBLT Study). The population was 60% male and the medical age was 5 years (range 0.05 to 68 years), and included patients treated for hematologic malignancies, inherited metabolic disorders, primary immunodeficiencies, and bone marrow failure. Preparative regimens and graft-versus-host disease prophylaxis were not standardized. The most common infusion reactions were hypertension, vomiting, nausea, and sinus bradycardia. Hypertension and any grades 3-4 infusion-related reactions occurred more frequently in patients receiving HPC, Cord Blood in volumes greater than 150 milliliters and in pediatric patients. The rate of serious adverse cardiopulmonary reactions was 0.8%.

Table 1: Incidence of Infusion-Related Adverse Reactions Occurring in ≥1% of Infusions (The COBLT Study)
 | Any Grade % | Grade 3-4 %
Any reaction | 65.4 | 27.6
Hypertension | 48.0 | 21.3
Vomiting | 14.5 | 0.2
Nausea | 12.7 | 5.7
Sinus bradycardia | 10.4 | 0
Fever | 5.2 | 0.2
Sinus Tachycardia | 4.5 | 0.2
Allergy | 3.4 | 0.2
Hypotension | 2.5 | 0
Hemoglobinuria | 2.1 | 0
Hypoxia | 2.0 | 2.0

Information on infusion reactions was available from voluntary reports for patients who received HPC, Cord Blood, with a total nucleated cell dose of ≥ 2.5 x 10^7/kg. Of 212 infusions, there were 22 reports of grade 3 or higher reactions at time of infusion (10.3%). The population included 59% males and 41% females with median age of 35 years (range <1-72 years). The most common infusion reactions in these patients were hypertension (63.6%), nausea (27.3%), and chest pain (18.2%). Preparative regimens and graft-vs-host disease prophylaxis were not standardized.

Other Adverse Reactions

For other adverse reactions, the raw clinical data from the docket were pooled for 1299 (120 adult and 1179 pediatric) patients transplanted with HPC, Cord Blood (from multiple cord blood banks) with total nucleated cells ≥ 2.5 x 10^7/kg. Of these, 66% (n=862) underwent transplantation treatment for hematologic malignancy. The preparative regimen and graft-versus-host disease prophylaxis varied. The median total nucleated cell dose was 6.4 x 10^7/kg (range, 2.5-73.8 x 10^7/kg). For these patients, Day-100 mortality from all causes was 25%. Primary graft failure occurred in 16%; 42% developed grades 2-4 graft-versus-host disease; and 19% developed grades 3-4 acute graft-versus-host disease.

Data from the published literature and from observational registries, institutional databases, and cord blood bank reviews reported to the docket for HPC, Cord Blood (from multiple cord blood banks) revealed nine cases of donor cell leukemia, one case of transmission of infection, and one report of transplantation from a donor with an inheritable genetic disorder. The data are insufficient to support reliable estimates of the incidences of these events.

In the COBLT Study, 15% of the patients developed engraftment syndrome.

8 USE IN SPECIFIC POPULATIONS

8.1 Pregnancy

Risk Summary

There are no data with HPC, Cord Blood use in pregnant women to inform a product-associated risk. Animal reproduction studies have not been conducted with HPC, Cord Blood. In the U.S. general population, the estimated background risk of major birth defects and miscarriage in clinically recognized pregnancies is 2-4% and 15-20%, respectively.

8.2 Lactation

Risk Summary

There is no information regarding the presence of HPC, Cord Blood in human milk, the effects on the breastfed infant, or the effects on milk production. The developmental and health benefits of breastfeeding should be considered along with the mother's clinical need for HPC, Cord Blood and any potential adverse effects on the breastfed infant from HPC, Cord Blood or from the underlying maternal condition.

8.4 Pediatric Use

HPC, Cord Blood has been used in pediatric patients with disorders affecting the hematopoietic system that are inherited, acquired, or resulted from myeloablative treatment. [See Dosage and Administration (2), Adverse Reactions (6), and Clinical Studies (14)].

8.5 Geriatric Use

Clinical studies of HPC, Cord Blood (from multiple cord blood banks) did not provide sufficient numbers of subjects aged 65 years and over to determine whether they respond differently than younger subjects. In general, administration of Bloodworks HPC, Cord Blood to patients over age 65 should be cautious, reflecting their greater frequency of decreased hepatic, renal or cardiac function, and concomitant disease or other drug therapy.

8.6 Renal Disease

HPC, Cord Blood contains Dextran 40 which is eliminated by the kidneys. The safety of HPC, Cord Blood has not been established in patients with renal insufficiency or renal failure.

10 OVERDOSAGE

10.1 Human Overdosage Experience

There has been no experience with overdosage of HPC, Cord Blood, in human clinical trials. Single doses of HPC, Cord Blood from Bloodworks of 29.6 x 10^7/kg have been administered. HPC, Cord Blood prepared for infusion may contain dimethyl sulfoxide (DMSO). The maximum dose of DMSO has not been established, but it is customary not to exceed a DMSO dose of 1 gm/kg/day when given intravenously. Several cases of altered mental status and coma have been reported with higher doses of DMSO.

10.2 Management of Overdose

For DMSO overdose, general supportive care is indicated. The role of other interventions to treat DMSO overdosage has not been established.

11 DESCRIPTION

HPC, Cord Blood consists of hematopoietic progenitor cells, monocytes, lymphocytes, and granulocytes from human cord blood for intravenous infusion. Blood recovered from umbilical cord and placenta is volume reduced and partially depleted of red blood cells and plasma.

The active ingredient is hematopoietic progenitor cells which express the cell surface marker CD34. The potency of the cord blood is determined by measuring the numbers of total nucleated cells (TNC) and CD34+ cells, and cell viability. Each unit of HPC, Cord Blood contains a minimum of 5 x 10^8 total nucleated cells with at least 1.25 x 10^6 viable CD34+ cells at the time of cryopreservation. The cellular composition of HPC, Cord Blood depends on the composition of cells in the blood recovered from the umbilical cord and placenta of the donor. The actual nucleated cell count, the CD34+ cell count, the ABO group, and the HLA typing are listed on the container label and/or accompanying records sent with each individual unit.

HPC, Cord Blood has the following inactive ingredients: dimethyl sulfoxide (DMSO), citrate phosphate dextrose (CPD), hydroxyethyl starch, and Dextran 40. When prepared for infusion according to instructions, the infusate contains the following inactive ingredients: Dextran 40, human serum albumin, DMSO, and CPD.

12 CLINICAL PHARMACOLOGY

12.1 Mechanism of Action

Hematopoietic stem/progenitor cells from HPC, Cord Blood migrate to the bone marrow where they divide and mature. The mature cells are released into the bloodstream, where some circulate and others migrate to tissue sites, partially or fully restoring blood counts and function, including immune function, of blood-borne cells of marrow origin. [See Clinical Studies (14)].

In patients with enzymatic abnormalities due to certain severe types of storage disorders, mature leukocytes resulting from HPC, Cord Blood transplantation may synthesize enzymes that may be able to circulate and improve cellular functions of some native tissues. However, the precise mechanism of action is unknown.

14 CLINICAL STUDIES

The effectiveness of Bloodworks HPC, Cord Blood, as defined by hematopoietic reconstitution, was demonstrated in one single-arm prospective study and in retrospective reviews of data from an observational database for Bloodworks, and in data in the dockets and public information. Of the 1299 patients in the dockets and public data, 66% (n=862) underwent transplantation as treatment for hematologic malignancy. Results for patients who received a total nucleated cell dose ≥ 2.5 x 10^7/kg are shown in Table 2. Neutrophil recovery is defined as the time from transplantation to an absolute neutrophil count more than 500 per microliter. Platelet count recovery is the time to a platelet count more than 20,000 per microliter. Erythrocyte recovery is the time to a reticulocyte count greater than 30,000 per microliter. The total nucleated cell dose and degree of HLA match were inversely associated with the time to neutrophil recovery in the docket data.

Table 2: Hematopoietic Recovery for Patients Transplanted with HPC, Cord Blood, COBLT and Docket Data Total Nucleated Cell (TNC) Dose ≥2.5 x 10^7/kg
Data Source | The COBLT Study* | Docket* and Public Data* | Bloodworks Cord Blood Program**
Design | Single-arm prospective | Retrospective | Retrospective
Number of patients | 324 | 1299 | Variable*
Median age (range) | 4.6 (0.07 – 52.2) yrs | 7.0 (<1 – 65.7) yrs | 35 (0 – 72) yrs
Gender | 59% male 41% female | 57% male 43% female | 59% male 41% female
Median TNC Dose (range) (x 10^7/kg) | 6.7 (2.6 – 38.8) | 6.4 (2.5 – 73.8) | 3.9 (2.5 – 42.3)β
Neutrophil Recovery at Day 42 (95% CI) | 76% (71% – 81%) | 77% (75% – 79%) | 82% (77% – 87%)
Platelet Recovery at Day 100 of 20,000/µL (95% CI) | 57% (51% – 63%) | - | 66% (60% – 72%)
Platelet Recovery at Day 100 of 50,000/µL (95% CI) | 46% (39% – 51%) | 45% (42% – 48%) | 50% (42% – 59%)
Erythrocyte Recovery at Day 100 (95% CI) | 65% (58% – 71%) | - | -
Median time to Neutrophil Recovery | 27 days | 25 days | 21.5 days
Median time to Platelet Recovery (20,000/µL) | 90 days | - | 46 days
Median time to Platelet Recovery (50,000/µL) | 113 days | 122 days | 53 days
Median time to Erythrocyte Recovery | 64 days | - | -
*FDA-1997-N-0010
**Sample size for median age = 468. N for gender = 468. Median TNC dose n = 194 (from units ≥ 2.5 x 10^7) Neutrophil data n = 339. For ≥20k Platelet n=328. N for 50k platelet = 267.
βMedian TNC dose (all doses) = 3.2 x 10^7

16 HOW SUPPLIED/STORAGE AND HANDLING

HPC, Cord Blood is supplied as a cryopreserved cell suspension in a sealed bag containing a minimum of 5 x 10^8 total nucleated cells with a minimum of 1.25 x 10^6 viable CD34+ cells in a volume of 25 milliliters (ISBT 128 Product Code S1393, ISBT 128 Facility Identifier Number W1640). The exact pre-cryopreservation nucleated cell content is provided on the container label and accompanying records.

Store HPC, Cord Blood at or below -150°C until ready for thawing and preparation.

17 PATIENT COUNSELING INFORMATION

Discuss the following with patients receiving HPC, Cord Blood.

- Report immediately any signs and symptoms of acute infusion reactions, such as fever, chills, fatigue, breathing problems, dizziness, nausea, vomiting, headache, or muscle aches.
- Report immediately any signs or symptoms suggestive of graft-versus-host disease, including rash, diarrhea, or yellowing of the eyes.

INSTRUCTIONS FOR PREPARATION FOR INFUSION

I. MATERIALS, REAGENTS, AND EQUIPMENT

Materials:

- Large zip-lock plastic bag (sterile interior is recommended)
- Sampling site couplers
- Tubing Clamps
- Sterile 300 mL Transfer Bag (labeled "LMD/25% HSA Solution #1")
- Sterile 300 mL Transfer Bag (labeled "LMD/5% HSA Solution #2")
- Sterile 300 mL Transfer Bag (labeled "Thawed Final Product")
- 14 gauge needles
- 3-5 inch blunt needle (a sterile spinal needle with trochar removed, if available) for emergency product recovery
- Sterile Syringes: 1, 10, 30 and 60 mL
- Sample tubes
- Isopropyl alcohol prep pads, 70% v/v
- Refrigerated gel packs
- Scissors

Reagents:

- 10% Low Molecular Weight Dextran-40 (LMD)
- Human Serum Albumin, USP (HSA), 25% and 5% Solution

Equipment:

- Refrigerator
- Biological Safety Cabinet
- Large water bath, 37°C ± 2°C
- Thermometer
- Di-electric sealer

NOTE: If performing wash step after dilution, then you will also need:

- Sterile Connecting Device
- Centrifuge blood bag adapter and insert (to support low volume bag)
- Centrifuge
- Manual Plasma Extractor
- Scale

Forms:

- Shipping Information
- CBU Summary sheet
- HPC, Cord Blood Release Specifications for Distribution
- HPC, Cord Blood Final Eligibility Determination
- NMDP Receipt of Cord Blood Unit

II. PRODUCT RECEIPT

The HPC, Cord Blood unit is shipped frozen in a dry-shipper that maintains the temperature at ≤ -150°C. The dry shipper is capable of maintaining the temperature of ≤ -150°C for 5 days from the shipping date. If the unit will not be used within that timeframe, transfer the unit into a storage device capable of maintaining the unit at ≤ -150°C.

Temperature during shipment is continuously monitored and a printout can be obtained upon request.

Handle the cryobag with extreme caution when removing it from the liquid nitrogen, metal cassette, and protective overwrap, and during the thaw procedure. Cryobags can be very fragile. This is applicable both during inspection of the product upon arrival and during the thawing process.

1. Upon receiving the shipper, perform the following steps:
  1. Inspect the shipper for tampering or damage prior to opening.
  2. Inspect the temperature monitor on the shipper; mark on the Shipping Information form which light is flashing: Normal, Warning, or Alarm.
    NOTE: If the Warning or Alarm light is flashing, immediately contact Bloodworks. See section VI, Contact Information.
  3. Open the shipper and remove the Tyvek envelope containing a cardboard box.
  4. Open the cardboard box and remove the metal cassette that contains the unit.
  5. Carefully open the cassette. The cassette will contain the unit (cryobag) sealed in an overwrap and padded in an absorbent sheet. Cracks or breakages in the overwrap do not indicate damage to the unit.
  6. Inspect the integrity of the cryobag.
    NOTE: If there is damage to cryobag, replace the cryobag into storage at ≤ -150°C (contain the cryobag in additional overwrap if necessary). Consult with the transplant physician and contact Bloodworks.
  7. Document location of inspection, identity of inspector, and date and time of inspection on the Shipping Information form.
  8. Verify that the unit ID number on the cryobag matches the unit ID number on all applicable paperwork, the unit ID number matches the expected unit for the intended recipient. Document verification on the Shipping Information form.
    NOTE: If there are any discrepancies in unit ID, consult with the transplant physician and contact Bloodworks.
    Store the product in an LN2 Storage vessel that maintains a temperature at or below -150°C.

III. PREPARATION

1. Initial preparation
  1. Coordinate with the clinical team
    1. Confirm the infusion time in advance. Adjust the start time for the thaw so that the unit is available for infusion when the recipient is ready.
    2. Consult with the clinicians about final product volume based on the recipient's weight and possible fluid restrictions, to determine if the Alternate Procedure (see Section IV.4) for DMSO removal and volume reduction should be followed.
  2. Perform clearance of workspace, including disinfection of lab bench and equipment.
  3. Prepare the water bath and verify the temperature is 37°C ± 2°C.
  4. Inspect LMD visually for particulate matter. If crystallization is observed, do not use and discard appropriately.
  5. Pre-cool the LMD, 25% and 5% HSA Solutions in the refrigerator.
  6. Prepare three sterile 300 mL transfer bags.
    1. Using a di-electric sealer, make three seals along the tubing close to the transfer bag, inspect seals for integrity and separate the tubing at the center seal.
      NOTE: If DMSO removal and volume reduction is required, for the 300mL transfer labeled "Thawed Final Product", seal tubing approximately 4-5 inches above the bag to allow for sterile connection in step IV.4.a.
    2. Place the transfer bags into the Biological Safety Cabinet. Insert a sampling coupler in each bag.
2. Prepare Solution #1 with 25% HSA/LMD in the Biological Safety Cabinet.
  1. With a syringe and needle, add 25 mL of cold LMD and 5 mL of cold 25% HSA (per each product being thawed) into a sterile, labeled 300 mL transfer bag.
  2. Mix Solution #1 by inverting and swirling the bag several times thoroughly without creating excessive bubbles.
  3. Store Solution #1 in refrigerator to cool.
    NOTE: The LMD/HSA Solution #1 must be used within 4 hours.
3. Prepare Solution #2 with 5% HSA/LMD in the Biological Safety Cabinet.
  1. With a syringe and needle, add 25 mL of the cold LMD and 25 mL of cold 5% HSA (per each product being thawed) into a sterile, labeled 300 mL transfer bag.
  2. Mix Solution #2 by inverting and swirling the bag several times thoroughly without creating excessive bubbles.
  3. Store Solution #2 in refrigerator to cool.
    NOTE: The LMD/HSA Solution #2 must be used within 4 hours.

IV. PROCEDURE

Reconstitution or simple dilution of HPC, Cord Blood with LMD/HSA solution, using the Thaw and Diluting procedures described below (steps IV.1-IV.3), is recommended. The Alternate Procedure: Washing in Section IV.4 should be followed if the infusion volume and/or DMSO dose (>1 g/kg body weight) are contraindicated for the patient.

1. Thaw HPC, Cord Blood
  1. Verify the identity of the HPC, Cord Blood being thawed.
  2. Using scissors that have been wiped down with alcohol, remove overwrap, detach any segments and store the segments at ≤ -150°C until needed.
  3. Wipe the external surface of the cryobag with isopropyl alcohol. Place the HPC, Cord Blood cryobag inside the large zip-lock plastic bag. Seal the bag closed.
    NOTE: Wiping the external surface of the cryobag with isopropyl alcohol before placing inside the sterile zip-lock bag allows the thawing laboratory to potentially recover the product in the case of an unexpected leak or container failure during thawing.
  4. Completely immerse the bag in the 37°C ± 2°C water bath.
  5. Gently agitate and knead the cryobag until the product reaches a slushy liquid consistency.
  6. Remove bag from the water bath and quickly inspect for tears or leaks.
    NOTE: If container integrity is observed to be compromised, position the cryobag and/or clamp with hemostats to prevent further escape of product. If visible cracks or breaks are observed, consult the transplant physician before proceeding. See Section V for Emergency Product Recovery procedures.
  7. Remove the thawed cryobag from zip-lock bag, wipe with alcohol, and place the cryobag into the Biological Safety Cabinet.
2. Transfer the thawed HPC, Cord Blood into a 300 mL Transfer Bag
  NOTE: Perform the transfer procedure in a Biological Safety Cabinet.
  1. Wipe down the cryobag port covers with alcohol to disinfect.
  2. Cut off port covers with scissors that have been wiped down with alcohol. Only cut through the outer layer of plastic. Do not cut the inner port column.
  3. Insert a sampling site coupler into each port using aseptic technique.
  4. Using a 30 mL syringe with a 14 gauge needle, aseptically withdraw the contents from both compartments into the syringe.
  5. Record the product volume removed (approximately 25 mL).
  6. Using an inserted sampling site coupler, slowly and aseptically transfer the product to a sterile 300 mL transfer bag (labeled as "Thawed Final Product").
  7. Place the product on refrigerated gel packs in the Biological Safety Cabinet.
3. Dilute HPC, Cord Blood
  NOTE: Perform the following dilution procedure in a Biological Safety Cabinet.
  1. Remove the 300 mL Transfer Bag containing Solution #1 from the refrigerator.
  2. Using a 60 mL syringe with a 14 gauge needle, aseptically fill the syringe with Solution #1 of a volume equal to the product volume noted in step 2.e (approximately 25 mL).
  3. Aseptically attach the 60 mL syringe containing Solution #1 to the 300 mL transfer bag containing the thawed product.
  4. Slowly add Solution #1 to the transfer bag while gently agitating the contents of the bag.
  5. Allow product to rest for 5 minutes. Maintain the bag chilled on refrigerated gel packs.
  6. Remove the 300 mL Transfer Bag containing Solution #2 from the refrigerator.
  7. Use a 60 mL syringe with a 14 gauge needle to aseptically fill the syringe with Solution #2, using two times the original product volume noted in step 2.e (approximately 50 mL).
  8. Aseptically attach the 60 mL syringe containing Solution #2 to the 300 mL transfer bag containing the product.
  9. Slowly add Solution #2 to the product while gently agitating the bag. Maintain the syringe and transfer bag chilled on refrigerated gel packs.
  10. Calculate the product volume from the volume noted in steps 2.e, the volume of Solution #1 from step 3.b, and the volume of Solution #2 in step 3.g.
  11. Aseptically remove samples for quality control tests (such as nucleated cell counts, viability testing, CD34 analysis, Colony Forming Units (CFU), and sterility testing) and transfer the samples into appropriately labeled tubes. Document the volume removed.
  12. Subtract the volume removed from the volume noted in step 3.j, thus determining the infusion volume. Document the infusion volume, which will be used for calculating cell numbers.
  13. Immediately transport the product to the clinical infusion site per the facility's SOP.
    NOTE: The recommended expiration time of thawed HPC, Cord Blood product is 4 hours from the time of thaw, if stored at 2-8°C.
4. Alternate Procedure: Washing (DMSO removal and volume reduction)
  Perform all steps of the Thaw and Transfer procedures, and steps 3.a through 3.i of the Dilute procedure as outlined above, and then complete the following steps:
  1. Sterile connect an empty sterile 300 mL transfer bag to the product bag from step 3.i. Place a tubing clip on the tubing close to the product bag.
  2. Place the thawed, diluted product bag and attached 300 mL transfer bag in a blood bag adapter with insert to support the low volume bag and centrifuge at 400 x g for 20 minutes at 4°C.
  3. Place the concentrated HPC, Cord Blood product bag in a manual plasma extractor.
  4. Place the attached empty 300 mL transfer bag on a scale and tare the scale.
  5. Remove the tubing clip. Use the plasma extractor to press off the supernatant into the attached transfer bag until approximately 20 mL cell pellet remains, and clamp the HPC, Cord Blood bag tubing.
  6. Resuspend the cell pellet by gentle agitation. In a Biological Safety Cabinet, use a 30 mL syringe to volumetrically measure the concentrated product. If necessary, add back supernatant to reach a final total volume of 20 mL.
  7. In a Biological Safety Cabinet, aseptically remove samples for quality control tests (such as nucleated cell counts, viability test, CD34 analysis, Colony Forming Units (CFU)) and transfer the samples into appropriately labeled tubes. Do not remove more than 500 microliters. Document the volume removed.
  8. Subtract the sample volume removed in step 4.g from the volume noted in step 4.f, thus determining the infusion volume. Document the infusion volume, which will be used for calculating cell numbers.
  9. In a Biological Safety Cabinet, aseptically add a sampling site coupler to the supernatant transfer bag and remove samples for sterility testing.
  10. Immediately transport the product to the clinical transport site per the facility's SOP.
    NOTE: The recommended expiration time of thawed HPC, Cord Blood product is 4 hours from the time of thaw, if stored at 2-8°C.

V. EMERGENCY PRODUCT RECOVERY IN THE EVENT OF A CONAINER FAILURE

1. Handle the cryobag with extreme caution when removing it from the liquid nitrogen, metal cassette, and protective overwrap and during the thaw proceudre. Cryobags can be very fragile. This is applicable both during inspection of the product upon arrival and during the thawing process.
2. Wipe the external surface of the cryobag with isopropyl alcohol before the cryobag is placed inside a sterile zip-lock bag. This process allows the thawing laboratory to potentially recover the product in the case of an unexpected leak or container failure during thawing or centrifugation.
3. Notify Bloodworks, the transplant physician/team, and local laboratory director immediately if any portion of the product or container seems to be damaged or compromised.
4. If the cryobag is compromised, move further handling into a Biological Safety Cabinet.
5. It is the physician's responsbility to determine whether the product will be used or discarded if the container is compromised at any step of the procedure. If the product is accepted for use, recovery of the product may be attempted as described below.
  1. Prepare an emptry transfer bag with a sampling site coupler.
  2. Use a long (3-5 inch) blunt needle (a sterile spinal needle with trochar removed, if available).
  3. Attach the blunt needle to a sterile 60 mL syringe.
  4. Aspirate the product, replace the blunt needle with a standard needle and inject it into a sterile transfer bag via a sampling site coupler.
  5. Continue processing of the transferred product from the point container failure was identified.
  6. Perform sterility testing on the product sample after final preparation step.

VI. CONTACT INFORMATION

Bloodworks
Cord Blood Services
921 Terry Ave.
Seattle, WA 98104

Hours: 7:30 AM - 6:00 PM, Pacific Standard Time
Phone Number: 206-689-6696
Alternate Phone Number: 1-800-366-2831, ext. 1896

After Hours
Cell Phone Number: 206-231-3108

Distributed by:
Bloodworks
Cord Blood Services
921 Terry Ave.
Seattle, WA 98104
License Number 2042

Principal Display Panel - Carton Label

"W1640 16 999999"

Product: S1393V00

HPC, CORD BLOOD

10% DMSO, Other additives present,
Cryopreserved, Buffy Coat Enriched

See Accompanying Documentation

Total Volume 25.13 mL

Store at -150 C or colder

Expires:

Bloodworks
921 Terry Ave
Seattle, WA 98104

Principal Display Panel - Bag Label

"W1640 16 999999"

Bloodworks
921 Terry Avenue
Seattle, WA 98104

Collection
Date/Time "0160281000"

28 Jan 2016 10:00 PST
(28 Jan, 2016 18:00 UTC)

Do Not Irradiate
Do Not Use Leukoreduction Filters
RX Only

"S1393V00"

HPC, CORD BLOOD

10% DMSO, Other additives present,
Cropreserved, Buffy Coat Enriched

See Accompanying Documentation

Total Volume 25.13 mL

Store at -150 C or colder

US License #: 2042

"6200"

A
Rh Positive

For Intravenous Administration

See package insert for full prescribing
information and instructions for
preparation.

Expiration
Date/Time
"0180281000"

28 Jan 2018 10:00 PST
(28 Jan, 2018 18:00 UTC)

Intended Recipient
Smith, Bob
Recipient ID: 9987-1234-5
Date of Birth: 04 Jul 1970